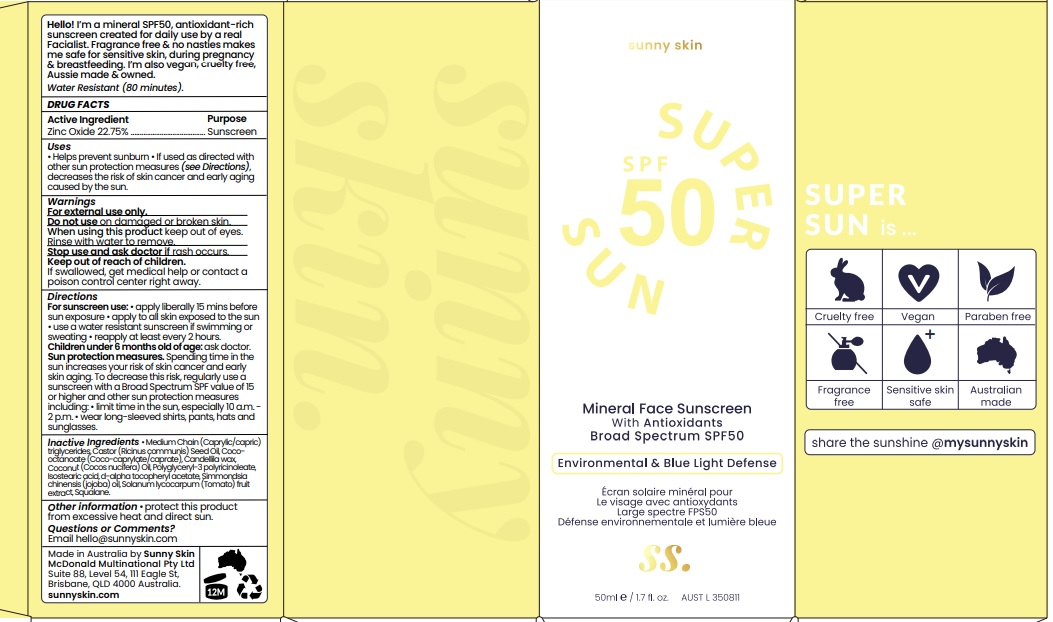 DRUG LABEL: Sunny Skin Super Sun SPF50
NDC: 83070-001 | Form: CREAM
Manufacturer: MCDONALD MULTINATIONAL PTY LTD
Category: otc | Type: HUMAN OTC DRUG LABEL
Date: 20221028

ACTIVE INGREDIENTS: ZINC OXIDE 22.75 g/100 mL
INACTIVE INGREDIENTS: MEDIUM-CHAIN TRIGLYCERIDES; CASTOR OIL; COCOYL CAPRYLOCAPRATE; CANDELILLA WAX; COCONUT OIL; POLYGLYCERYL-3 PENTARICINOLEATE; ISOSTEARIC ACID; .ALPHA.-TOCOPHEROL ACETATE, D-; JOJOBA OIL; SOLANUM LYCOCARPUM FRUIT; SQUALANE

Active ingredient

Zinc Oxide 22.75%

Purpose

Mineral Sunscreen

Uses

Help Prevent Sunburn. If uses as directed with other sun protection measures (see directions) decreases the risk of skin cancer and early ageing caused by the sun

Warnings

For external Use Only.

Do not Use on damaged or broken Skin.

When using this product keep out of eyes. Rinse with water to remove.

Stop use and ask doctor is rash occurs.

Keep out of reach of children. If swallowed, get medical help or contact a poison control centre right away.

Directions

For sunscreen use: • apply liberally 15 mins before sun exposure • apply to all skin exposed to the sun • use a water resistant sunscreen if swimming or sweating • reapply at least every 2 hours.
Children under 6 months old of age: ask doctor. Sun protection measures. Spending time in the sun increases your risk of skin cancer and early skin aging. To decrease this risk, regularly use a sunscreen with a Broad Spectrum SPF value of 15 or higher and other sun protection measures including: • limit time in the sun, especially 10 a.m. - 2 p.m. • wear long-sleeved shirts, pants, hats and sunglasses.

Inactive Ingredients

MediumChain(Caprylic/capric) triglycerides, Castor (Ricinus communis) Seed Oil, Coco-octanoate (Coco-caprylate/caprate), Coconut (Cocos nucifera) Oil, Candellila wax, Hydrogenated castor oil, polyglyceryl-3 polyricinoleate, Tocopheryl acetate, Iron oxides, isostearic acid, IBR-TCLC in Jojoba Oil 0705 (Simmondsia Chinensis (Jojoba) Seed Oil (and) Squalane (and) Solanum Lycopersicum (Tomato) Fruit Extract).

Other information

protect this product from excessive heat and direct sun.

Questions or Comments?
Email hello@sunnyskin.com